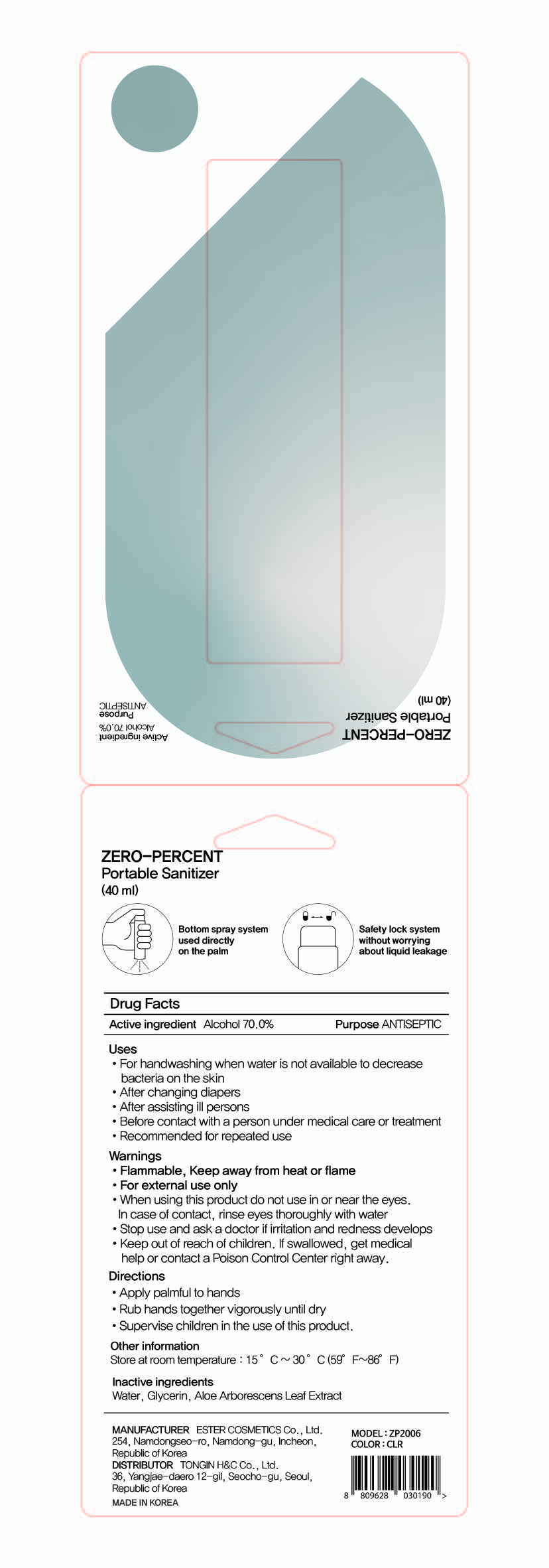 DRUG LABEL: ZERO-PERCENT Portable Sanitizer
NDC: 74004-042 | Form: SPRAY
Manufacturer: Ester Co., Ltd.
Category: otc | Type: HUMAN OTC DRUG LABEL
Date: 20201006

ACTIVE INGREDIENTS: ALCOHOL 28 mL/40 mL
INACTIVE INGREDIENTS: GLYCERIN; ALOE ARBORESCENS LEAF; WATER

[2] ZERO-PERCENT Portable Sanitizer (Fragrance-free)
74004-042-02
Blister pakage